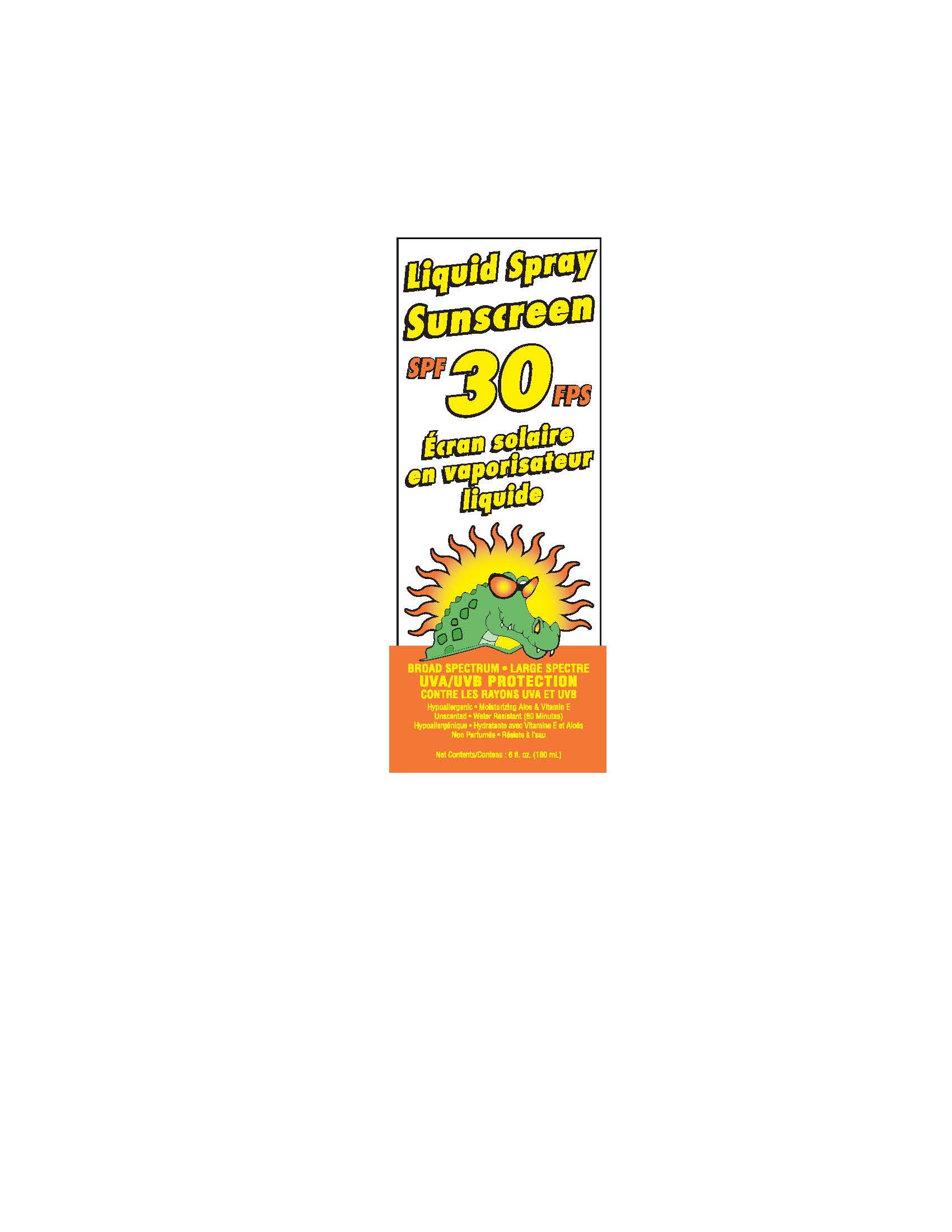 DRUG LABEL: CROC BLOC SPF 30 FPS ECRAN SOLAIRE
NDC: 58331-301 | Form: LIQUID
Manufacturer: Degil Safety Products (1989) Inc.
Category: otc | Type: HUMAN OTC DRUG LABEL
Date: 20200526

ACTIVE INGREDIENTS: OCTISALATE 4 g/100 g; AVOBENZONE 2 g/100 g; OCTINOXATE 7.5 g/100 g; OXYBENZONE 4 g/100 g; OCTOCRYLENE 1.5 g/100 g
INACTIVE INGREDIENTS: STEARYL ALCOHOL; POLYOXYL 20 CETOSTEARYL ETHER; MICROCRYSTALLINE CELLULOSE; EDETATE DISODIUM ANHYDROUS; PROPYLENE GLYCOL; DIAZOLIDINYL UREA; METHYLPARABEN; ALPHA-TOCOPHEROL ACETATE; DECYL GLUCOSIDE; METHYL GLUCOSE SESQUISTEARATE; POLYESTER-8 (1400 MW, CYANODIPHENYLPROPENOYL CAPPED); ALOE VERA LEAF; TROLAMINE; PROPYLPARABEN; PEG-20 METHYL GLUCOSE SESQUISTEARATE; WATER; ISODODECANE; CARBOXYMETHYLCELLULOSE

Drug Facts

ACTIVE INGREDIENT

Octinoxate | 7.5% w/w | Sunscreen
Octisalate | 4.0% w/w | Sunscreen
Oxybenzone | 4.0% w/w | Sunscreen
Avobenzone | 2.0% w/w | Sunscreen
Octocylene | 1.5% w/w | Sunscreen

PURPOSE

Active Ingredients |  | Purposes
Octinoxate | 7.5% w/w | Sunscreen
Octisalate | 4.0% w/w | Sunscreen
Oxybenzone | 4.0% w/w | Sunscreen
Avobenzone | 2.0% w/w | Sunscreen
Octocylene | 1.5% w/w | Sunscreen

Warnings

For external use only

May stain or damage some fabrics or surfaces.

DO NOT USE

on damaged or broken skin

KEEP OUT OF REACH OF CHILDREN

If swallowed, get medical help or contact a Poison Control Center right away.

WHEN USING

Avoid contact with eyes. Rinse with water to remove.

STOP USE

Rash and irritation develops and lasts

Directions

Apply liberally and evenly to dry skin 15 minutes belofe going Into the sun. Reapply at least fN8ry 2 houlS. Reapply after 80 minutes of swimming or sweating. Reapply lmmetlatety after towel drying.
• For children under 6 months of age: Ask a doctor

Other Information

Sun Protection Measures: Spending time in the sun increases your risk of skin cancer and early skin aging. To decrease this risk, regularly use a sunscreen with a Broad Spectrum SPF value of 15 or higher and other sun protection measures inciucling: limit time In the sun, especially from 10 a.m.-2 p.m.; and Wear long-sleeved shirts, pants, hats, and sunglasses. lf used as directed with
other sun protection measures (See Dlrections), decreases the risk of skin cancer and early skin aging caused by the sun. Protect container from freezing.

INACTIVE INGREDIENT

Aqua, Aloe Barbadensis Leaf Exlract, lsododecane, Acrylates/C12-22 Alkyl Methacrylate Copolymer, Methyl Glucose Sesquistearate, PEG-20 Methyl Glucose Sesquistearate, Polyester-8. PVP/Hexadecene Copolymer, Tocopheryl Acetate, Decyl Glucoside. Stearyl Alcohol, Ceteareth-20, Microcrystalline Cellulose, Cellulose Gum, Propylene Glycol, Disodium EDTA, Triethanolamine, Diazolidinyl Urea, Methylparaben, Propylparaben.

PRINCIPAL DISPLAY PANEL

Liquid Spray

Sunscreen

SPF 30 FPS

Ecran solaire

en vaporisateur

liquide

BROAD SPECTRUM • LARGE SPECTRE

UVA/UVB PROTECTION

CONTRE LES RAYONS UVA ET UVB

Hypoallergic • Moisturizing Aloe & Vitamin E

Unscented • Water Resistant (80 minutes)

Hypoallergenique • Hydratante avec Vitamine E et Aloes

Non Parfumee • Resiste a l'eau